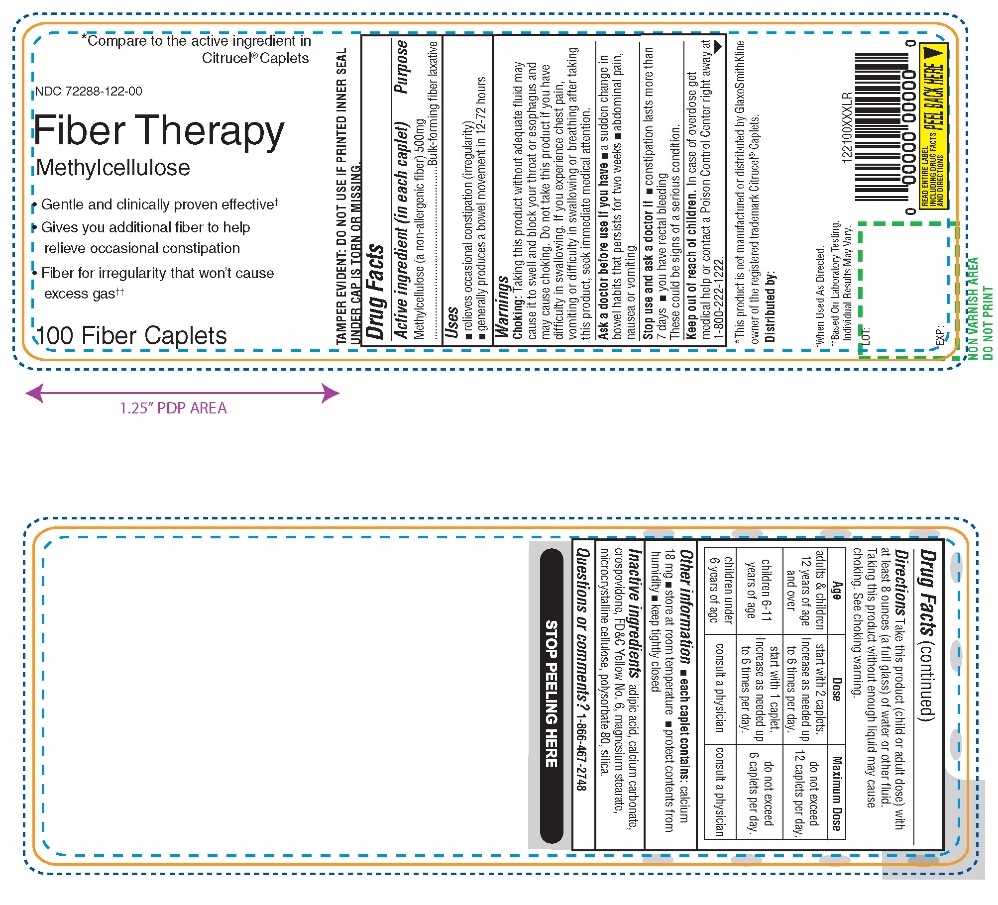 DRUG LABEL: AMAZON
NDC: 72288-122 | Form: TABLET
Manufacturer: AMAZON.COM SERVICES LLC
Category: otc | Type: HUMAN OTC DRUG LABEL
Date: 20251222

ACTIVE INGREDIENTS: METHYLCELLULOSE (4000 MPA.S) 500 mg/1 1
INACTIVE INGREDIENTS: ADIPIC ACID; CALCIUM CARBONATE; CROSPOVIDONE (120 .MU.M); FD&C YELLOW NO. 6; MAGNESIUM STEARATE; MICROCRYSTALLINE CELLULOSE; POLYSORBATE 80; SILICON DIOXIDE

Fiber Therapy Methylcellulose 500 mg 100 Caplets

Active ingredient (in each caplet)

Methylcellulose (a non-allergenic fiber) 500 mg

Purpose

Bulk-forming laxative

Uses

- Relieves occasional constipation (irregularity)
- Generally produces a bowel movement in 12-72 hours

Warnings

Choking: Taking this product without adequate fluid may cause it to swell and block your throat or esophagus and may cause choking. Do not take this product if you have difficulty in swallowing. If you experience chest pain, vomiting or difficulty in swallowing or breathing after taking this product, seek immediate medical attention.

Ask a doctor before use if you have

- a sudden change in bowel habits that persists for 2 weeks
- abdominal pain, nausea or vomiting

Stop use and ask a doctor if

- constipation lasts more than 7 days
- You have rectal bleeding
  These could be signs of a serious condition.

Keep out of reach of children.

In case of overdose, get medical help or contact a Poison Control Center right away at 1-800-222-1222.

Directions

Take this product (child or adult dose) with at least 8 ounces (a full glass) of water or other fluid. Taking this product without enough liquid may cause choking.

See choking warning.

AGE | DOSE | MAXIMUM DOSE
adults & children 12 years of age and over | Start with 2 caplets. Increase as needed up to 6 times per day. | do not exceed 12 caplets per day.
children 6 to 11 years of age | Start with 1 caplet. Increase as needed up to 6 times per day. | do not exceed 6 caplets per day.
children under 6 years of age | consult a physician | consult a physician

Other information

- each caplet contains: calcium 18 mg
- store at room temperature
- protect contents from humidity
- keep tightly closed

Inactive ingredients

adipic acid, calcium carbonate, crospovidone, FD&C yellow no. 6, magnesium stearate, microcrystalline cellulose, polysorbate 80, silica.

Questions or comments?

1-866-467-2748

Principal Display Panel

*Compare to the active ingredient in Citrucel® Caplets

NDC 72288-122-00

Fiber Therapy

Methylcellulose

- Gentle and clinically proven effective†
- Gives you additional fiber to help relieve occasional constipation
- Fiber for irregularity that won’t cause excess gas††

100 Fiber Caplets

TAMPER EVIDENT: DO NOT USE IF PRINTED INNER SEAL UNDER CAP IS TORN OR MISSING.

†When Used As Directed

††Based On Laboratory Testing.

Individual Results May Vary.

Distributed by:

*This product is not manufactured or distributed by GlaxoSmithKline, the owner of the registered trademark Citrucel® Caplets.